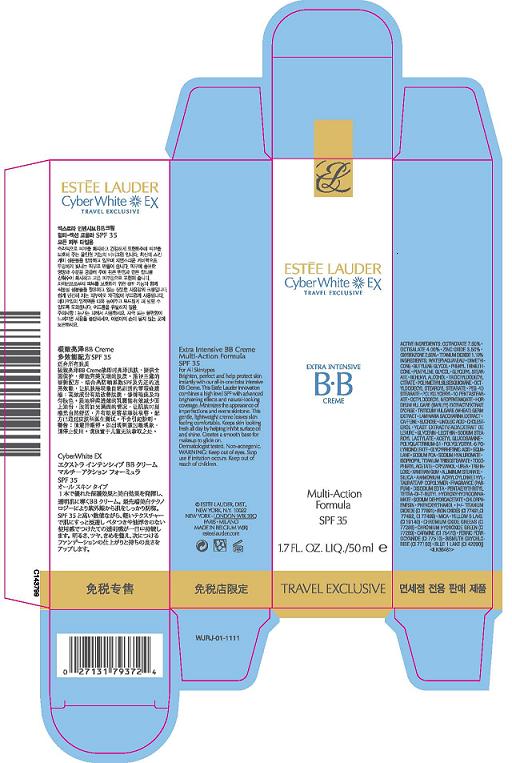 DRUG LABEL: CYBERWHITE EX
NDC: 11559-004 | Form: CREAM
Manufacturer: ESTEE LAUDER INC
Category: otc | Type: HUMAN OTC DRUG LABEL
Date: 20100413

ACTIVE INGREDIENTS: OCTINOXATE 7.5 mL/100 mL; OCTISALATE 4.0 mL/100 mL; ZINC OXIDE 3.5 mL/100 mL; OXYBENZONE 2.5 mL/100 mL; TITANIUM DIOXIDE 1.1 mL/100 mL

ACTIVE INGREDIENT

ACTIVE INGREDIENTS: OCTINOXATE 7.50% [] OCTISALATE 4.00% [] ZINC OXIDE 3.50% [] OXYBENZONE 2.50% [] TITANIUM DIOXIDE 1.10%

WARNINGS

WARNING: KEEP OUT OF EYES. STOP USE IF IRRITATION OCCURS. KEEP OUT OF REACH OF CHILDREN.

PACKAGE LABEL

PRINCIPAL DISPLAY PANEL

ESTEE LAUDER
CYBER WHITE EX
EXTRA INTENSIVE BB CREME
MULTI-ACTION
FORMULA
SPF 35
1.7 FL OZ. LIQ./50 ML
ESTEE LAUDER DIST.
NEW YORK, NY 10022
ESTEELAUDER.COM
WJRJ